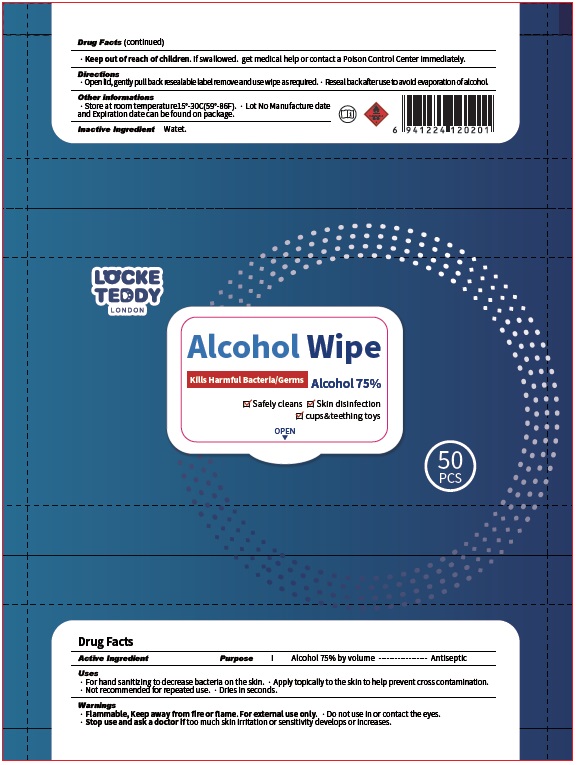 DRUG LABEL: Locke Teddy
NDC: 73928-006 | Form: SWAB
Manufacturer: KINGKEY MBC LIFE TECHNOLOGY GROUP CO., LTD
Category: otc | Type: HUMAN OTC DRUG LABEL
Date: 20251007

ACTIVE INGREDIENTS: ALCOHOL 75 mL/100 mL
INACTIVE INGREDIENTS: WATER

Active Ingredient

Alcohol 75% by volume

Purpose

Antiseptic

Uses

- For hand sanitizing to decrease bacteria on the skin.
- Apply topically to the skin to help prevent cross contamination.
- Not recommended for repeated use.
- Dries in seconds.

Warnings

Flammable, Keep away from fire or flame. For external use only.
Do not use in or contact the eyes.
Stop use and ask a doctor iftoo much skin irritation or sensitivity develops or increases.

Keep out of reach of children.If swallowed, get medical help or contact a Poison Control Center right away.

Directions

- Open lid, gently pull back resealable label remove and use wipe as required.
- Reseal back after use to avoid evaporation of alcohol

Other information

- Store between 15-30oC (59-86oF)
- Lot No Manufacture date and Expiration date can be found on package.

Inactive ingredients

Water